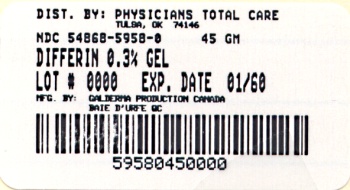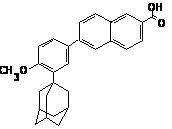 DRUG LABEL: DIFFERIN 
NDC: 54868-5958 | Form: GEL
Manufacturer: Physicians Total Care, Inc.
Category: prescription | Type: HUMAN PRESCRIPTION DRUG LABEL
Date: 20120307

ACTIVE INGREDIENTS: Adapalene 3 mg/1 g
INACTIVE INGREDIENTS: Carbomer Homopolymer Type C; Edetate Disodium; Methylparaben; Propylene Glycol; Water; Sodium Hydroxide; Hydrochloric Acid; Poloxamer 124

HIGHLIGHTS OF PRESCRIBING INFORMATION

These highlights do not include all the information needed to use DIFFERIN safely and effectively. See full prescribing information for DIFFERIN (adapalene) Gel, 0.3% DIFFERIN (adapalene) Gel, 0.3% For topical use only Initial U.S. Approval: 1996

1 INDICATIONS AND USAGE

DIFFERIN Gel, 0.3%, is a retinoid, indicated for the topical treatment of acne vulgaris in patients 12 years of age and older. (1)

2 DOSAGE AND ADMINISTRATION

Apply a thin film of DIFFERIN Gel, 0.3% to the entire face and any other affected areas of the skin once daily in the evening, after washing gently with a non-medicated soap. (2)
For topical use only. Not for ophthalmic, oral or intravaginal use. (2)

3 DOSAGE FORMS AND STRENGTHS

Each gram of DIFFERIN Gel, 0.3% contains 3 mg adapalene in an off-white aqueous gel. (3)

4 CONTRAINDICATIONS

DIFFERIN Gel, 0.3% should not be administered to individuals who are hypersensitive to adapalene or any of the components in the gel vehicle. (4)

5 WARNINGS AND PRECAUTIONS

Ultraviolet Light and Environmental Exposure: Avoid exposure to sunlight and sunlamps. Wear sunscreen when sun exposure cannot be avoided. (5.1) Erythema, scaling, dryness, and stinging/burning were reported with use of DIFFERIN Gel. (5.2)

6 ADVERSE REACTIONS

The most frequently reported (≥ 1%) adverse reactions were dry skin, skin discomfort, pruritus, desquamation, and sunburn. (6.1)
To report SUSPECTED ADVERSE REACTIONS, contact Galderma Laboratories, L.P. at 1-866-735-4137 or FDA at 1-800-FDA-1088 or www.fda.gov/medwatch.

7 DRUG INTERACTIONS

As DIFFERIN Gel has the potential to induce local irritation in some patients, concomitant use of other potentially irritating topical products (medicated or abrasive soaps and cleansers, soaps and cosmetics that have a strong drying effect, and products with high concentrations of alcohol, astringents, spices, or lime) should be approached with caution. Use with caution, especially when using preparations containing sulfur, resorcinol, or salicylic acid in combination with DIFFERIN Gel. (7)

FULL PRESCRIBING INFORMATION

1 INDICATIONS AND USAGE

DIFFERIN Gel, 0.3% is indicated for the topical treatment of acne vulgaris in patients 12 years of age and older.

2 DOSAGE AND ADMINISTRATION

Apply a thin film of DIFFERIN Gel, 0.3% to the entire face and any other affected areas of the skin once daily in the evening, after washing gently with a non-medicated soap. Avoid application to the areas of skin around eyes, lips, and mucous membranes. A mild transitory sensation of warmth or slight stinging may occur shortly after the application of DIFFERIN Gel, 0.3%. Patients should be instructed to minimize sun exposure. Patients may be instructed to use moisturizers for relief of dry skin or irritation.

If therapeutic results are not noticed after 12 weeks of treatment, therapy should be re-evaluated.

For topical use only. Not for ophthalmic, oral or intravaginal use.

3 DOSAGE FORMS AND STRENGTHS

Each gram of DIFFERIN Gel, 0.3% contains 3 mg adapalene in an off-white aqueous gel.

4 CONTRAINDICATIONS

DIFFERIN Gel, 0.3% should not be administered to individuals who are hypersensitive to adapalene or any of the components in the gel vehicle.

5 WARNINGS AND PRECAUTIONS

5.1 Ultraviolet Light and Environmental Exposure

Exposure to sunlight, including sunlamps, should be minimized during use of DIFFERIN Gel, 0.3%. Patients who normally experience high levels of sun exposure, and those with inherent sensitivity to sun, should be warned to exercise caution. Use of sunscreen products and protective clothing over treated areas is recommended when exposure cannot be avoided. Weather extremes, such as wind or cold, also may be irritating to patients under treatment with DIFFERIN Gel, 0.3%.

5.2 Local Cutaneous Reactions

Certain cutaneous signs and symptoms of treatment such as erythema, scaling, dryness, and stinging/burning were reported with use of DIFFERIN Gel, 0.3%. These were most likely to occur during the first four weeks of treatment, were mostly mild to moderate in intensity, and usually lessened with continued use of the medication. Depending upon the severity of these side effects, patients should be instructed to either use a moisturizer, reduce the frequency of application of DIFFERIN Gel, 0.3% or discontinue use.

Avoid contact with the eyes, lips, angles of the nose, and mucous membranes. The product should not be applied to cuts, abrasions, eczematous or sunburned skin. As with other retinoids, use of "waxing" as a depilatory method should be avoided on skin treated with adapalene.

As DIFFERIN Gel has the potential to induce local irritation in some patients, concomitant use of other potentially irritating topical products (medicated or abrasive soaps and cleansers, soaps and cosmetics that have a strong drying effect and products with high concentrations of alcohol, astringents, spices, or lime) should be approached with caution.

5.3 Allergic/ Hypersensitivity Reactions

Reactions characterized by symptoms such as pruritus, face edema, eyelid edema, and lip swelling, requiring medical treatment have been reported during postmarketing use of adapalene. A patient should stop using DIFFERIN Gel, 0.3% and consult a doctor if experiencing allergic or anaphylactoid/anaphylactic reactions (e.g., skin rash, pruritus, hives, chest pain, edema, and shortness of breath) during treatment.

6 ADVERSE REACTIONS

6.1 Clinical Studies Experience

Because clinical studies are conducted under widely varying conditions, adverse reactions rates observed in the clinical studies of a drug cannot be directly compared to rates in the clinical studies of another drug and may not reflect the rates observed in practice.

In the multi-center, controlled clinical trial, signs and symptoms of local cutaneous irritation were monitored in 258 acne patients who used DIFFERIN Gel, 0.3% once daily for 12 weeks. Of the patients who experienced cutaneous irritation (erythema, scaling, dryness, and/or burning/stinging), the majority of cases were mild to moderate in severity, occurred early in treatment and decreased thereafter. The incidence of local cutaneous irritation with DIFFERIN Gel, 0.3% from the controlled clinical study is provided in the following table:

Table 1: Physician assessed local cutaneous irritation with DIFFERIN Gel
Incidence of Local Cutaneous Irritation with DIFFERIN Gel, 0.3% from Controlled Clinical Study
(N = 253*)
Maximum Severity Scores Higher Than Baseline
 | Mild | Moderate | Severe
Erythema | 66 (26.1%) | 33 (13.0%) | 1 (0.4%)
Scaling | 110 (43.5%) | 47 (18.6%) | 3 (1.2%)
Dryness | 113 (44.7%) | 43 (17.0%) | 2 (0.8%)
Burning/Stinging | 72 (28.5%) | 36 (14.2%) | 9 (3.6%)

* Total number of subjects with local cutaneous data for at least one post-Baseline evaluation.

Table 2: Patient reported local cutaneous adverse reactions with DIFFERIN Gel
 | DIFFERIN (adapalene) Gel, 0.3% | Vehicle Gel
 | N=258 | N=134
Related* Adverse Reactions | 57 (22.1%) | 6 (4.5%)
Dry Skin | 36 (14%) | 2 (1.5%)
Skin Discomfort | 15 (5.8%) | 0 (0.0%)
Desquamation | 4 (1.6%) | 0 (0.0%)

* Selected adverse reactions defined by investigator as Possibly, Probably or Definitely Related

Related adverse reactions from the controlled clinical trial that occurred in greater than 1% of patients who used DIFFERIN Gel, 0.3% once daily included: dry skin (14.0%), skin discomfort (5.8%), pruritus (1.9%), desquamation (1.6%), and sunburn (1.2%). The following selected adverse reactions occurred in less than 1% of patients: acne flare, contact dermatitis, eyelid edema, conjunctivitis, erythema, pruritus, skin discoloration, rash, and eczema.

In a one-year, open-label safety study of 551 patients with acne who received DIFFERIN Gel, 0.3%, the pattern of adverse reactions was similar to the 12-week controlled study.

6.2 Postmarketing Experience

The following adverse reactions have been identified during post approval use of adapalene: skin irritation, application site pain, face edema, eyelid edema, lip swelling, and angioedema. Because these reactions are reported voluntarily from a population of uncertain size, it is not always possible to reliably estimate the frequency or establish a causal relationship to drug exposure.

7 DRUG INTERACTIONS

Concomitant Topical Medications
As DIFFERIN Gel, 0.3% has the potential to induce local irritation in some patients, concomitant use of other potentially irritating topical products (medicated or abrasive soaps and cleansers, soaps and cosmetics that have a strong drying effect, and products with high concentrations of alcohol, astringents, spices, or lime) should be approached with caution. Particular caution should be exercised in using preparations containing sulfur, resorcinol, or salicylic acid in combination with DIFFERIN Gel, 0.3%. If these preparations have been used, it is advisable not to start therapy with DIFFERIN Gel, 0.3%, until the effects of such preparations have subsided.

No formal drug-drug interaction studies were conducted with DIFFERIN Gel, 0.3%.

8 USE IN SPECIFIC POPULATIONS

8.1 Pregnancy

Teratogenic effects. Pregnancy Category C.
Retinoids may cause fetal harm, when administered to pregnant women. Adapalene has been shown to be teratogenic in rats and rabbits when administered orally (see Animal Data below). There are no adequate and well-controlled studies in pregnant women. DIFFERIN Gel, 0.3% should be used during pregnancy only if the potential benefit justifies the potential risk to the fetus. The safety and efficacy of DIFFERIN Gel, 0.3% in pregnancy has not been established.

Human Data

In clinical trials involving DIFFERIN Gel, 0.3% in the treatment of acne vulgaris, women of child-bearing potential initiated treatment only after having had a negative pregnancy test and used effective birth control measures during therapy. However, 6 women treated with DIFFERIN Gel, 0.3% became pregnant. One patient elected to terminate the pregnancy, two patients delivered healthy babies by normal delivery, two patients delivered prematurely and the babies remained in intensive care until reaching a healthy state and one patient was lost to follow-up.

Animal Data

- No teratogenic effects were seen in rats at oral doses of 0.15 to 5.0 mg/kg/day adapalene representing up to 6 times the maximum recommended human dose (MRHD) based on mg/m² comparisons. Adapalene has been shown to be teratogenic in rats and rabbits when administered orally at doses ≥ 25 mg/kg representing 32 and 65 times, respectively, the MRHD based on mg/m² comparisons. Findings included cleft palate, microphthalmia, encephalocele and skeletal abnormalities in the rat and umbilical hernia, exophthalmos and kidney and skeletal abnormalities in the rabbit.
- Cutaneous teratology studies in rats and rabbits at doses of 0.6, 2.0, and 6.0 mg/kg/day exhibited no fetotoxicity and only minimal increases in supernumerary ribs in both species and delayed ossification in rabbits. Systemic exposure (AUC0-24h) to adapalene 0.3% gel at topical doses of 6.0 mg/kg/day in rats and rabbits represented 5.7 and 28.7 times, respectively, the exposure in acne patients treated with adapalene 0.3% gel applied to the face, chest and back (2 grams applied to 1000 cm^2 of acne involved skin).

8.3 Nursing Mothers

It is not known whether adapalene is excreted in human milk. Because many drugs are excreted in human milk, caution should be exercised when DIFFERIN Gel, 0.3% is administered to a nursing woman.

8.4 Pediatric Use

Safety and effectiveness have not been established in pediatric patients below the age of 12.

8.5 Geriatric Use

Clinical studies of DIFFERIN Gel, 0.3% did not include subjects 65 years of age and older to determine whether they respond differently than younger subjects. Safety and effectiveness in geriatric patients age 65 and above have not been established.

10 OVERDOSAGE

DIFFERIN Gel, 0.3% is intended for topical use only. If the medication is applied excessively, no more rapid or better results will be obtained and marked redness, scaling, or skin discomfort may occur. Chronic ingestion of the drug may lead to the same side effects as those associated with excessive oral intake of vitamin A.

11 DESCRIPTION

DIFFERIN (adapalene) Gel, 0.3% contains adapalene 0.3% (3 mg/g) in a topical aqueous gel for use in the treatment of acne vulgaris, consisting of carbomer 940, edetate disodium, methylparaben, poloxamer 124, propylene glycol, purified water, and sodium hydroxide. May contain hydrochloric acid for pH adjustment.

The chemical name of adapalene is 6-[3-(1-adamantyl)-4-methoxyphenyl]-2-naphthoic acid. It is a white to off-white powder, which is soluble in tetrahydrofuran, very slightly soluble in ethanol, and practically insoluble in water. The molecular formula is C28H28O3 and molecular weight is 412.53. Adapalene is represented by the following structural formula.

12 CLINICAL PHARMACOLOGY

12.1 Mechanism of Action

Adapalene binds to specific retinoic acid nuclear receptors but does not bind to cytosolic receptor protein. Biochemical and pharmacological profile studies have demonstrated that adapalene is a modulator of cellular differentiation, keratinization, and inflammatory processes. However, the significance of these findings with regard to the mechanism of action of adapalene for the treatment of acne is unknown.

12.2 Pharmacodynamics

Clinical pharmacodynamic studies have not been conducted for Differin Gel, 0.3%.

12.3 Pharmacokinetics

Systemic exposure of adapalene following topical application of DIFFERIN Gel was evaluated in a clinical study. Sixteen acne patients were treated once daily for 10 days with 2 grams of DIFFERIN Gel, 0.3% applied to the face, chest and back, corresponding to approximately 2 mg/cm^2. Fifteen patients had quantifiable (LOQ = 0.1 ng/mL) adapalene levels resulting in a mean Cmax of 0.553 ± 0.466 ng/mL on Day 10 of treatment. The mean AUC0-24hr was 8.37 ± 8.46 ng.h/mL as determined in 15 of the 16 patients on Day 10. The terminal apparent half-life, determined in 15 of 16 patients, ranged from 7 to 51 hours, with a mean of 17.2 ± 10.2 hours. Adapalene was rapidly cleared from plasma and was not detected 72 hours after the last application for all but one subject. Exposure of potential circulating metabolites of adapalene was not measured. Excretion of adapalene appears to be primarily by the biliary route.

In another clinical study in patients with moderate to moderately severe acne, DIFFERIN (adapalene) Gel, 0.3% or Adapalene Gel, 0.1% was applied to the face and optionally to the trunk, once daily for 12 weeks. Seventy-eight (78) patients had plasma adapalene levels evaluated at Weeks 2, 8, and 12. Of the 209 plasma samples analyzed, adapalene concentrations were below the limit of detection (LOD = 0.15 ng/mL) of the method in all samples but three. For the three samples, traces of adapalene below the limit of quantification (LOQ = 0.25 ng/mL) of the method were found. One of these samples was taken at Week 12 from a male patient treated with DIFFERIN Gel, 0.3% who treated the face and the trunk for eight weeks (thereafter, only the face was treated). The second and third samples were from the Week 2 and 12 visits of a female patient treated with Adapalene Gel, 0.1% who treated only the face for 12 weeks. In this study, the average daily usage of product was 1 g/day.

13 NONCLINICAL TOXICOLOGY

13.1 Carcinogenesis, Mutagenesis, Impairment of Fertility

Carcinogenicity studies with adapalene have been conducted in mice at topical doses of 0.4, 1.3, and 4.0 mg/kg/day, and in rats at oral doses of 0.15, 0.5, and 1.5 mg/kg/day. These doses are up to 3 times (mice) and 2 times (rats) in terms of mg/m²/day the potential exposure at the maximum recommended human dose (MRHD), assumed to be 2.5 grams DIFFERIN Gel, 0.3%. In the oral study, increased incidence of benign and malignant pheochromocytomas in the adrenal medullas of male rats was observed.

No photocarcinogenicity studies were conducted. Animal studies have shown an increased risk of skin neoplasms with the use of pharmacologically similar drugs (e.g., retinoids) when exposed to UV irradiation in the laboratory or to sunlight. Although the significance of these studies to human use is not clear, patients should be advised to avoid or minimize exposure to either sunlight or artificial UV irradiation sources.

Adapalene did not exhibit mutagenic or genotoxic effects in vitro (Ames test, Chinese hamster ovary cell assay, mouse lymphoma TK assay) and in vivo (mouse micronucleus test).

Reproductive function and fertility studies were conducted in rats administered oral doses of adapalene in amounts up to 20 mg/kg/day (up to 26 times the MRHD based on mg/m² comparisons). No effects of adapalene were found on the reproductive performance or fertility of the F0 males or females. There were also no detectable effects on the growth, development and subsequent reproductive function of the F1 offspring.

14 CLINICAL STUDIES

The safety and efficacy of once daily use of DIFFERIN Gel, 0.3% for treatment of acne vulgaris were assessed in one 12 week, multi-center, controlled, clinical study, conducted in a total of 653 patients 12 to 52 years of age with acne vulgaris of mild to moderate severity. All female patients of child-bearing potential enrolled in the study were required to have a negative urine pregnancy test at the beginning of the study and were required to practice a highly effective method of contraception during the study. Female patients who were pregnant, nursing or planning to become pregnant were excluded from the study.

Patients enrolled in the study were Caucasian (72%), Hispanic (12%), African-American (10%), Asian (3%), and other (2%). An equal number of males (49.5%) and females (50.5%) enrolled. Success was defined as "Clear" or "Almost Clear" in the Investigator’s Global Assessment (IGA). The success rate, mean reduction, and percent reduction in acne lesion counts from Baseline after 12 weeks of treatment are presented in the following table:

Table 3: Clinical study primary efficacy results at Week 12
 |  | DIFFERIN (adapalene) Gel, 0.3% | Adapalene Gel, 0.1% | Vehicle Gel
 |  | N=258 | N=261 | N=134
IGA Success Rate |  | 53 (21%) | 41 (16%) | 12 (9%)
Inflammatory Lesions
 | Mean Baseline Count | 27.7 | 28.1 | 27.2
 | Mean Absolute (%) Reduction | 14.4 (51.6%) | 13.9 (49.7%) | 11.2 (40.7%)
Non-inflammatory Lesions
 | Mean Baseline Count | 39.4 | 41.0 | 40.0
 | Mean Absolute (%) Reduction | 16.3 (39.7%) | 15.2 (35.2%) | 10.3 (27.2%)
Total Lesions
 | Mean Baseline Count | 67.1 | 69.1 | 67.2
 | Mean Absolute (%) Reduction | 30.6 (45.3%) | 29.0 (41.8%) | 21.4 (33.7%)

16 HOW SUPPLIED/ STORAGE AND HANDLING

DIFFERIN Gel, 0.3% is supplied in the following size.
45g tube – NDC 54868-5958-0

Storage: Store at controlled room temperature 68° to 77°F (20° to 25°C) with excursions permitted between 59° to 86°F (15° to 30°C). Protect from freezing. Keep out of reach of children.

17 PATIENT COUNSELING INFORMATION

17.1 Information for Patients

Patients using DIFFERIN Gel, 0.3%, should receive the following information and instructions:

1. This medication is to be used only as directed by the physician.
2. Do not use more than the recommended amount and do not apply more than once daily as this will not produce faster results, but may increase irritation.
3. Apply a thin film of DIFFERIN Gel, 0.3% to the entire face and any other affected areas of the skin once daily in the evening, after washing gently with a non-medicated soap.
4. Avoid contact with the eyes, lips, angles of the nose, and mucous membranes.
5. Moisturizers may be used if necessary; however, products containing alpha hydroxy or glycolic acids should be avoided.
6. Exposure of the eye to this medication may result in reactions such as swelling, conjunctivitis, and eye irritation.
7. This medication should not be applied to cuts, abrasions, eczematous, or sunburned skin.
8. Wax depilation should not be performed on treated skin due to the potential for skin erosions.
9. Minimize exposure to sunlight including sunlamps. Recommend the use of sunscreen products and protective apparel (e.g., hat) when exposure cannot be avoided.
10. During the early weeks of therapy, an apparent exacerbation of acne may occur. This may be due to the action of the medication on previously unseen lesions and should not be considered a reason to discontinue therapy.
11. Contact the doctor if skin rash, pruritus, hives, chest pain, edema, and shortness of breath occurs, as these may be signs of allergy or hypersensitivity.
12. It is for external use only.

Marketed by:
GALDERMA LABORATORIES, L.P.
Fort Worth, Texas 76177 USA

Manufactured by:
DPT Laboratories, Ltd.
San Antonio, Texas 78215 USA
GALDERMA is a registered trademark.
325089-0810

Manufactured by:
G Production Inc.
Baie d’Urfe´, QC, H9X 3S4 Canada
Made in Canada
GALDERMA is a registered trademark.
P51238-1

Additional barcode labeling by:
Physicians Total Care, Inc.
Tulsa, Oklahoma 74146

PACKAGE LABEL

Differin® 0.3
(adapalene)gel, 0.3%

GEL

0.3%

NDC 54868-5958-0

Rx Only

NET WT. 45 g

For external use only. Not for ophthalmic, oral, or intravaginal use.

Usual dosage: apply a thin film once a day at nighttime to affected areas. See package insert for complete prescribing information.

Each gram contains: adapalene 0.3% (3 mg) in an aqueous gel consisting of carbomer 940, edetate disodium, methylparaben, poloxamer 124, propylene glycol, purified water, and sodium hydroxide. May contain hydrochloric acid for pH adjustment.

Storage: Store at controlled room temperature 68° to 77°F (20° to 25°C) with excursions permitted between 59° to 86°F (15° to 30°C). Protect from freezing.